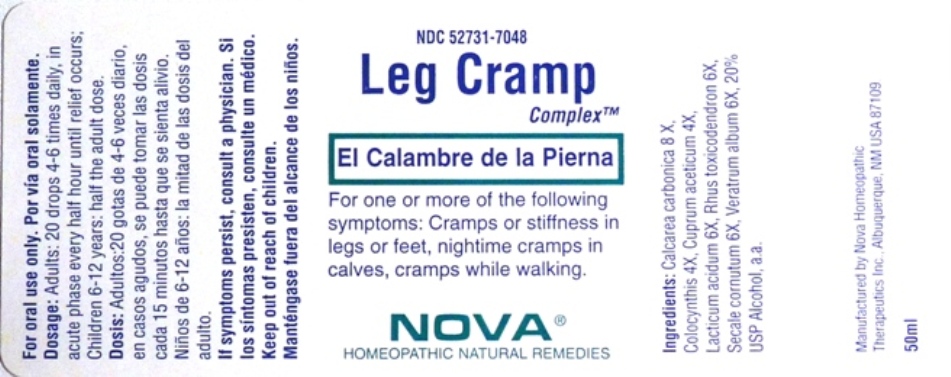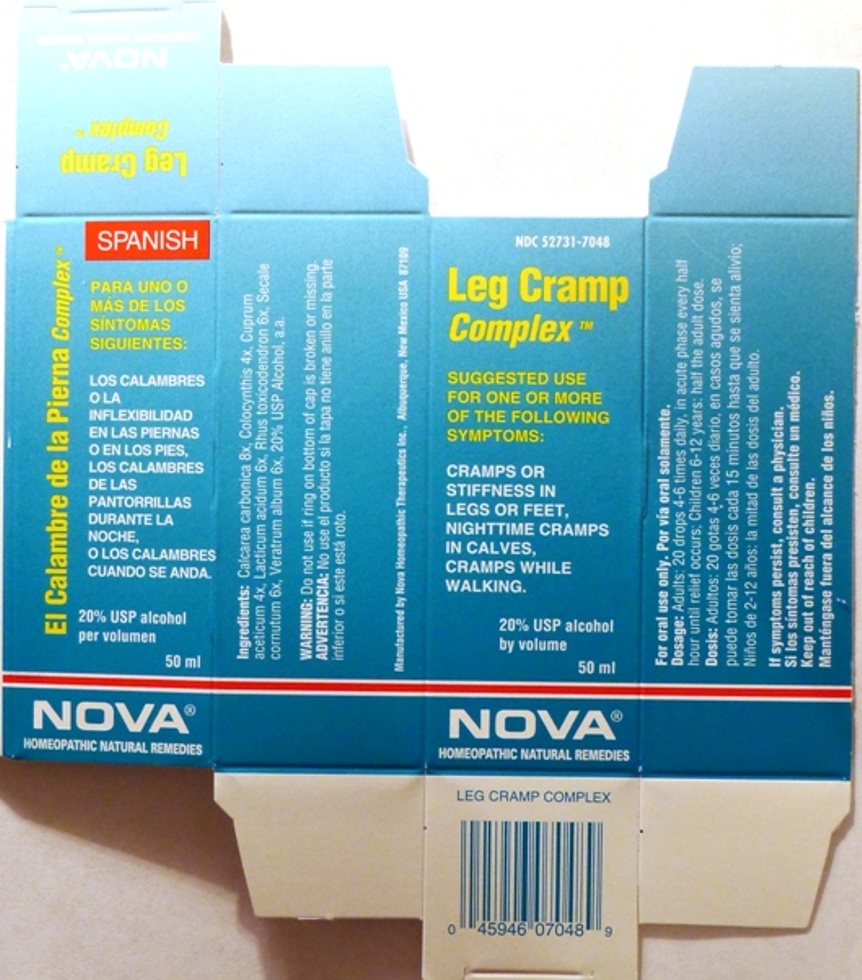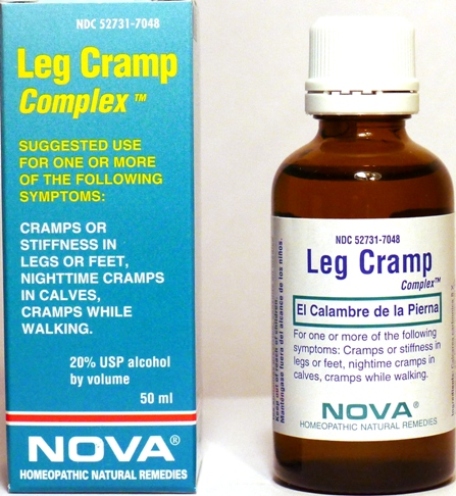 DRUG LABEL: Leg Cramp Complex
NDC: 52731-7048 | Form: LIQUID
Manufacturer: Nova Homeopathic Therapeutics, Inc.
Category: homeopathic | Type: HUMAN OTC DRUG LABEL
Date: 20110601

ACTIVE INGREDIENTS: OYSTER SHELL CALCIUM CARBONATE, CRUDE 8 [hp_X]/1 mL; CITRULLUS COLOCYNTHIS FRUIT PULP 4 [hp_X]/1 mL; CUPRIC ACETATE 4 [hp_X]/1 mL; LACTIC ACID, DL- 6 [hp_X]/1 mL; TOXICODENDRON PUBESCENS LEAF 6 [hp_X]/1 mL; CLAVICEPS PURPUREA SCLEROTIUM 6 [hp_X]/1 mL; VERATRUM ALBUM ROOT 6 [hp_X]/1 mL
INACTIVE INGREDIENTS: ALCOHOL

Leg Cramp Complex

Purpose:

Suggested use for one or more of the following symptoms:

Cramps or stiffness in legs or feet, nighttime cramps in calves, cramps while walking.

Usage and Dosage:

For oral use only.

DOSAGE AND ADMINISTRATION

Adults:
In Acute Phase:
20 drops, every half hour until relief occurs
When Relief Occurs:
12-15 drops, 4-6 times per day

Children 6-12 years:
10 drops, 4-6 times per day

Warnings:

Keep out of reach of children.

WARNINGS

If symptoms persist, consult a physician.
Do not use if ring on bottom of cap is broken or missing.

Active Ingredients:

Calcarea carbonica 8x, Colocynthis 4x, Cuprum aceticum 4x, Lacticum acidum 6x, Rhus toxicodendron 6x, Secale cornutum 6x, Veratrum album 6x

Inactive Ingredients:

Alcohol, 20% USP

QUESTIONS

Manufactured by Nova Homeopathic Therapeutics Inc., Albuquerque, New Mexico USA 87109
1-800-225-8094

PACKAGE LABEL

Leg Cramp Complex Product

Leg Cramp Complex Bottle Label

Leg Cramp Complex Box